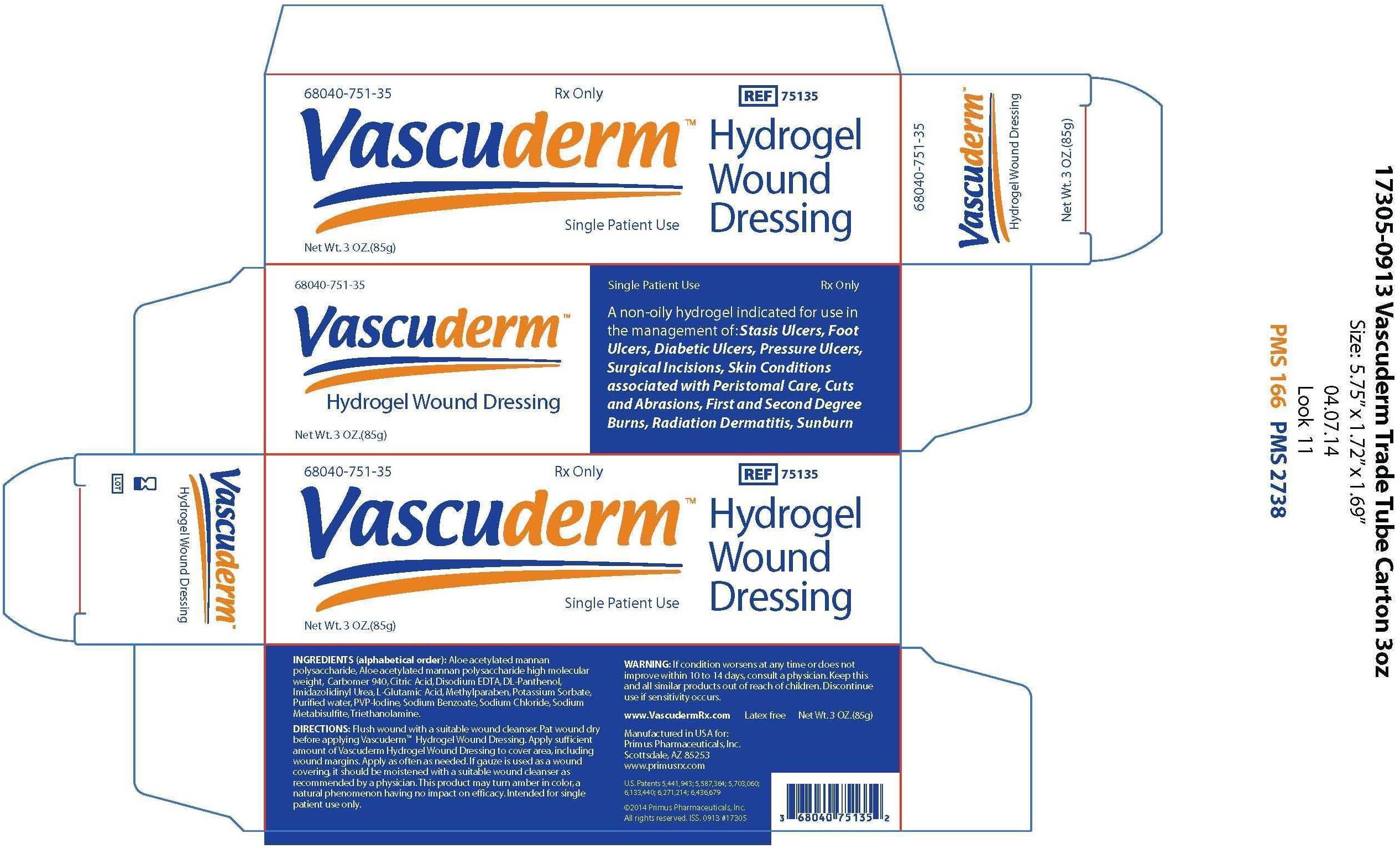 DRUG LABEL: VASCUDERM Hydrogel Wound Dressing
NDC: 68040-751
Manufacturer: Primus Pharmaceuticals, Inc
Category: other | Type: MEDICAL DEVICE
Date: 20141118

Home Use Medical Device

Description

VASCUDERM Hydrogelgel Wound Dressing is a non-oily hydrogel intended for the management of wounds.

Ingredients

Aloe acetylated mannan polysaccharide, Aloe acetylated mannan polysaccharide high molecular weight, Carbomer 940, Citric acid, Disodium EDTA, DL-Panthenol, Imidazolidinyl urea, L-glutamic acid, Methylparaben, Potassium sorbate, Purified water, PVP, Sodium benzoate, Sodium chloride, Sodium metabisulfite, Triethanolamine.

Summary of Safety and Effectiveness

The product is for topical use. The safety of the gel was established through standard biocompatibility tests. These biocompatibility tests were conducted in standard animal models with preparation of the VASCUDERM Hydrogel Wound Dressing. These tests included Primary Dermal Irritation testing and Primary Eye Irritation testing. These studies demonstrated that Vascuderm hydrogel are not primary dermal irritants or primary eye irritants. These studies were conducted in conformance with Good Laboratory Practices (GLP) regulations of the United States Food and Drug Administration (21 CFR, Part 58).

Clinical experience to date has been grained during the course of two studies that involved four patients with radiation dermatitis and 30 with diabetic ulcers. Grades III or IV disbetic ulcers of the foot were treated with VASCUDERM Hydrogel Wound Dressing for 10 weeks. Acute and subacute radiation dermatitis was treated for various times with VASCUDERM Hydrogel Wound Dressing. These studies evaluated the acceptablity of VASCUDERM Hydrogel Wound Dressing to both patients and clinicians, to wound and skin appearance, and to the wound healing environment. These studies concluded that VASCUDERM Hydrogel Wound Dressing is safe and effective for its intended use.

Indications

VASCUDERM Hydrogel Wound Dressing is indicated for use in the management of: Stasis Ulcers, Foot Ulcers, Diabetic Ulcers, Pressure Ulcers, Surgical Incisions, Skin Conditions associated with Peristomal Care, Cuts and Abrasions, First and Second Degree Burns, Radiation Dermatitis, and Sunburn.

Directions for Use

Flush wound with a suitable wound cleanser. Pat wound dry before applying VASCUDERM Hydrogel Wound Dressing. Apply sufficient amount of VASCUDERM Hydrogel Wound Dressing to cover area, including wound margins. Apply as often as needed. If gauze is used as a wound covering, it should be moistened with a suitable wound cleanser as recommended by a physician.

This product may turn amber in color, a natural phenomenon having no impact on efficacy. Intended for single patient use only.

PRECAUTION: Reduce the possibility of contamination by restricting use of each individual tube of VASCUDERM Hydrogel Wound Dressing to only one patient.

Warnings

If condition worsens or does not improve within 10-14 days, consult a physician. Keep this and all similar products out of the reach of children. Discontinue use if sensitivity occurs.

Adverse Reactions

Sensitivity to VASCUDERM Hydrogel Wound Dressing is infrequent. If a reaction is observed, discontinue use and consult a physician. Consult a physician for assistance with wounds that do not heal normally.

How Supplied

Package # | Description
68040-751-35 | 85 gram tube
68040-751-04 | 5 gram pouch sample - not for resale

Each 5 gram sample pouch contains multiple doses depending on the surface area treated.

Storage

Store in a dry place and at room temerature.